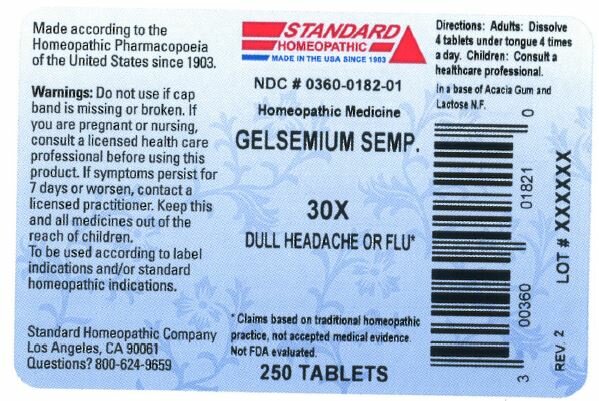 DRUG LABEL: GELSEMIUM SEMPERVIRENS
NDC: 0360-0182 | Form: TABLET
Manufacturer: STANDARD HOMEOPATHIC COMPANY
Category: homeopathic | Type: HUMAN OTC DRUG LABEL
Date: 20181228

ACTIVE INGREDIENTS: GELSEMIUM SEMPERVIRENS ROOT 30 [hp_X]/1 g
INACTIVE INGREDIENTS: ACACIA; LACTOSE MONOHYDRATE

GELSEMIUM SEMP. 30X

Made according to the
Homeopathic Pharmacopoeia
of the United States since 1903.

Warnings

Do not use if cap band is missing or broken.

If you are pregnant or nursing, consult a licensed health care professional before using this product.

If symptoms persist for 7 days or worsen, contact a licensed practitioner.

To be used according to label indications and/or standard homeopathic indications

KEEP OUT OF REACH OF CHILDREN

Keep this and all medicines out of the reach of children.

QUESTIONS

Standard Homeopathic Company
Los Angeles, CA 90061
Questions? 800-624-9659

Directions

Adults: Dissolve 4 tablets under tongue 4 times a day.
Children: Consult a healthcare professional

INACTIVE INGREDIENT

In a base of Acacia Gum and Lactose N.F.

ACTIVE INGREDIENT

GELSEMIUM SEMP. 30X

INDICATIONS AND USAGE

PURPOSE

DULL HEADACHE OR FLU

Principal Display Panel -- 250 Tablet Bottle Label

Standard

Homeopathic

Made in the USA Since 1903

NDC # 0360-0182-01

Homeopathic Medicine

GELSEMIUM SEMP.

30X

DULL HEADACHE OR FLU*

*Claims based on traditional homeopathic

practice, not accepted medical evidence.

Not FDA evaluated.

250 TABLETS